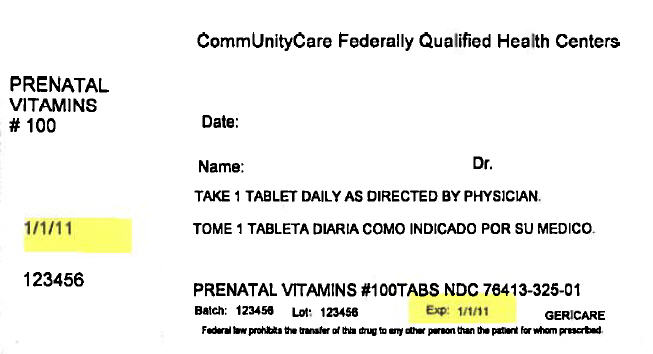 DRUG LABEL: Prenatal
NDC: 76413-325 | Form: TABLET, COATED
Manufacturer: Central Texas Community Health Centers
Category: other | Type: DIETARY SUPPLEMENT
Date: 20170929

ACTIVE INGREDIENTS: Vitamin A Palmitate 4000 [iU]/1 1; Ascorbic Acid 120 mg/1 1; Cholecalciferol 400 [iU]/1 1; .Alpha.-Tocopherol Acetate 30 [iU]/1 1; Thiamine Mononitrate 1.8 mg/1 1; Riboflavin 1.7 mg/1 1; Niacinamide 20 mg/1 1; Pyridoxine Hydrochloride 2.6 mg/1 1; Folic acid 0.8 mg/1 1; Cyanocobalamin 8 ug/1 1; Calcium Carbonate 200 mg/1 1; Ferrous fumarate 28 mg/1 1; Zinc oxide 25 mg/1 1
INACTIVE INGREDIENTS: powdered cellulose; croscarmellose sodium; magnesium stearate; hypromellose, unspecified; POLYETHYLENE GLYCOL, UNSPECIFIED; mineral oil; titanium dioxide; talc; FD&C Red NO. 40; FD&C Yellow NO. 6; FD&C Blue NO. 2

PRENATAL VITAMINS

SAFE HANDLING WARNING

TAMPER EVIDENT: Do not use if imprinted safety seal under cap is broken or missing

STATEMENT OF IDENTITY

Supplement Facts
Serving Size: 1 Tablet
 | Amount Per Serving | % DV [% Daily Value for Pregnant and Lactating Women]
Vitamin A (Palmitate) | 4000 IU | 50%
Vitamin C (Ascorbic Acid) | 120 mg | 200%
Vitamin D (Cholecalciferol) | 400 IU | 100%
Vitamin E (dl - Alpha Tocopheryl Acetate) | 30 IU | 100%
Vitamin B-1 (Thiamine Mononitrate) | 1.8 mg | 106%
Vitamin B-2 (Riboflavin) | 1.7 mg | 85%
Niacin (Niacinamide) | 20 mg | 100%
Vitamin B-6 (Pyridoxine HCl) | 2.6 mg | 104%
Folic Acid | 0.8 mg | 100%
Vitamin B-12 (Cyanocobalamin) | 8 mcg | 100%
Calcium (Calcium Carbonate) | 200 mg | 15%
Iron (Ferrous Fumarate) | 28 mg | 156%
Zinc (Oxide) | 25 mg | 167%

Other ingredients: cellulose, croscarmellose sodium, magnesium stearate, hypromellose, PEG, mineral oil, titanium dioxide, talc, FD&C Red #40, FD&C Yellow #6, FD&C Blue #2

INDICATIONS

For use as a dietary supplement prior to conception, during pregnancy and during the postnatal period, for both the nursing and non-nursing mother.

DIRECTIONS

For adults, one tablet daily, preferably with food. Ask your health care provider before taking any supplements or medications.

WARNINGS

WARNING: Accidental overdose of iron-containing products is a leading cause of fatal poisoning in children under six.
KEEP THIS PRODUCT OUT OF REACH OF CHILDREN
In case of accidental overdose, call a doctor or Poison Control Center immediately.

HEALTH CLAIM

Store at room temperature (59° - 86°F).

REV 0615

DIST. BY: GERI-CARE
PHARMACEUTICALS CORP.
1650 63rd Street
Brooklyn, NY 11204

PRINCIPAL DISPLAY PANEL - 100 Tablet Bottle Label

CommUnityCare Federally Qualified Health Centers

PRENATAL
VITAMINS
# 100

Date:

Name:
Dr.

TAKE 1 TABLET DAILY AS DIRECTED BY PHYSICIAN.

1/1/11

123456

PRENATAL VITAMINS #100TABS NDC 76413-325-01

Batch:
123456
Lot:
123456
Exp:
1/1/11

GERICARE

Federal law prohibits the transfer of this drug to any other person than the patient for whom prescribed.